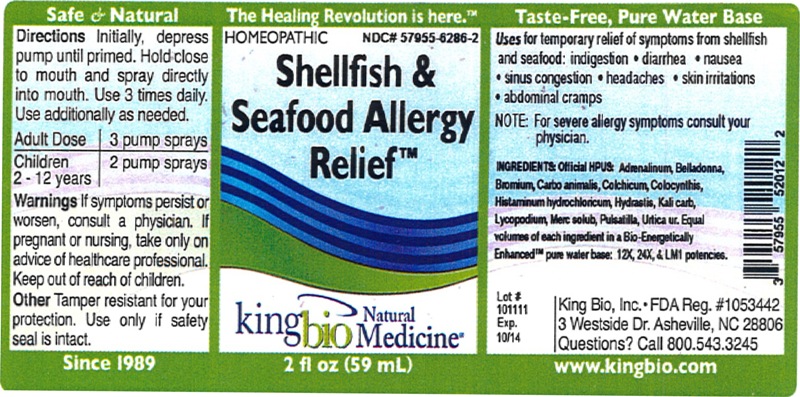 DRUG LABEL: Shellfish and Seafood Allergy Relief
NDC: 57955-6286 | Form: LIQUID
Manufacturer: King Bio Inc.
Category: homeopathic | Type: HUMAN OTC DRUG LABEL
Date: 20120622

ACTIVE INGREDIENTS: EPINEPHRINE 12 [hp_X]/59 mL; ATROPA BELLADONNA 12 [hp_X]/59 mL; BROMINE 12 [hp_X]/59 mL; CARBO ANIMALIS 12 [hp_X]/59 mL; COLCHICUM AUTUMNALE BULB 12 [hp_X]/59 mL; CITRULLUS COLOCYNTHIS FRUIT PULP 12 [hp_X]/59 mL; HISTAMINE DIHYDROCHLORIDE 12 [hp_X]/59 mL; GOLDENSEAL 12 [hp_X]/59 mL; POTASSIUM CARBONATE 12 [hp_X]/59 mL; LYCOPODIUM CLAVATUM SPORE 12 [hp_X]/59 mL; MERCURIUS SOLUBILIS 12 [hp_X]/59 mL; PULSATILLA VULGARIS 12 [hp_X]/59 mL; URTICA URENS 12 [hp_X]/59 mL
INACTIVE INGREDIENTS: WATER

Shellfish and Seafood Allergy Relief

Active Ingredients

Official HPUS: Adrenalinum, Belladonna, Bromium, Carbo animalis, Colchicum autumnale, Colocynthis, Histaminum hydrochloricum, Hydrastis canadensis, Kali carbonicum, Lycopodium clavatum, Mercurius solubilis, Pulsatilla, Urtica urens.

Reference image shellfishandseafoodallergyrelief.jpg

Inactive Ingredient

Equal volumes of each ingredient in a Bio-Energetically Enhanced pure water base: 12X, 24X, and LM1 potencies.

Reference image shellfishandseafoodallergyrelief.jpg

Purposes

Uses for temporary relief of symptoms from shellfish and seafood:

- Indigestion
- Diarrhea
- Nausea
- Sinus Congestion
- Headaches
- Skin Irritations
- Abdominal Cramps

NOTE: For severe allergy symptoms consult your physician.
Reference image shellfishandseafoodallergyrelief.jpg

Dosage and Administration

Directions: Initially, depress pump until primed. Hold close to mouth and spray directly into mouth. Use 3 times daily. Use additionally as needed.

Adult Dose - 3 Pump Sprays

Children 2-12 Years - 2 Pump Sprays

Reference image shellfishandseafoodallergyrelief.jpg

Warnings

Warnings If symptoms persist or worsen, consult a physician. If pregnant or nursing, take only on advice of healthcare professional.

Other Tamper resistant for your protection. Use only if safety seal is intact.

Reference image shellfishandseafoodallergyrelief.jpg

Keep out of reach of children.

Reference image shellfishandseafoodallergyrelief.jpg

Indications and Usage

Uses for temporary relief of symptoms from shellfish and seafood: indigestion, diarrhea, nausea, sinus congestion, headaches, skin irritations, abdominal cramps.

Reference image shellfishandseafoodallergyrelief.jpg

PACKAGE LABEL

King Bio, Inc.

3 Westside DR

Asheville, NC 28806

Questions? Call 800.543.3245

www.kingbio.com

Reference image shellfishandseafoodallergyrelief.jpg